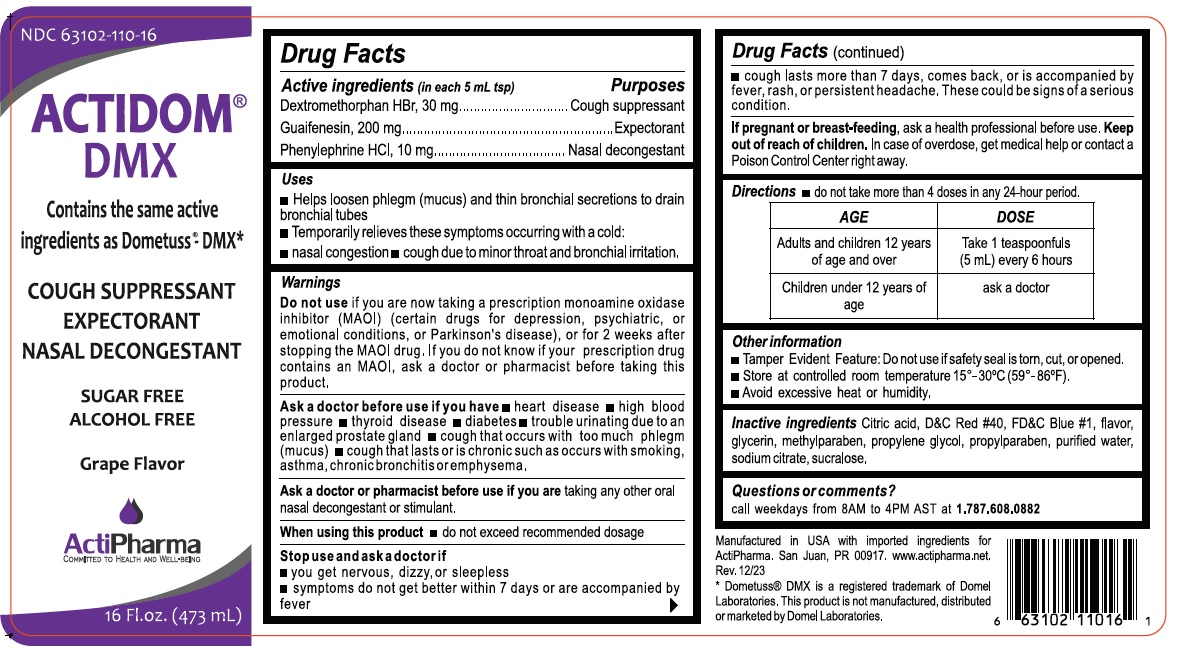 DRUG LABEL: ACTIDOM DMX
NDC: 63102-110 | Form: SOLUTION
Manufacturer: ACTIPHARMA, LLC
Category: otc | Type: HUMAN OTC DRUG LABEL
Date: 20240628

ACTIVE INGREDIENTS: DEXTROMETHORPHAN HYDROBROMIDE 30 mg/5 mL; GUAIFENESIN 200 mg/5 mL; PHENYLEPHRINE HYDROCHLORIDE 10 mg/5 mL
INACTIVE INGREDIENTS: CITRIC ACID MONOHYDRATE; FD&C RED NO. 40; FD&C BLUE NO. 1; GLYCERIN; METHYLPARABEN; PROPYLENE GLYCOL; PROPYLPARABEN; WATER; SODIUM CITRATE, UNSPECIFIED FORM; SUCRALOSE

ACTIDOM DMX

Active ingredients (in each 5 mL tsp)

Dextromethorphan HBr, 30 mg
Guaifenesin, 200 mg
Phenylephrine HCl, 10 mg

Purposes

Cough suppressant
Expectorant
Nasal decongestant

Uses

• Helps loosen phlegm (mucus) and thin bronchial secretions to drain bronchial tubes
• Temporarily relieves these symptoms occurring with a cold:
• nasal congestion • cough due to minor throat and bronchial irritation.

Warnings

Do not use if you are now taking a prescription monoamine oxidase inhibitor (MAOI) (certain drugs for depression, psychiatric, or emotional conditions, or Parkinson’s disease), or for 2 weeks after stopping the MAOI drug. If you do not know if your prescription drug contains an MAOI, ask a doctor or pharmacist before taking this product.

Ask a doctor before use if you have • heart disease • high blood pressure • thyroid disease • diabetes • trouble urinating due to an enlarged prostate gland • cough that occurs with too much phlegm (mucus) • cough that lasts or is chronic such as occurs with smoking, asthma, chronic bronchitis or emphysema.

Ask a doctor or pharmacist before use if you are taking any other oral nasal decongestant or stimulant.

When using this product • do not exceed recommended dosage

Stop use and ask a doctor if
• you get nervous, dizzy or sleepless
• symptoms do not get better within 7 days or are accompanied by fever
• coughs lasts more than 7 days, comes back, or is accompanied by fever, rash, or a persistent headache. These could be signs of a serious condition.

If pregnant or breast-feeding, ask a health professional before use.

Keep out of reach of children. In case of overdose, get medical help or contact a Poison Control Center right away.

Directions

• do not take more than 4 doses in any 24-hour period.

AGE | DOSE
Adults and Children 12 years; of age and over | Take 1 teaspoonfuls; (5 mL) every 6 hours
Children under 12 years of; age | ask a doctor

Other information

• Tamper Evident Feature: Do not use if safety seal is torn, cut or opened.
• Store at controlled room temperature 15° - 30ºC (59º - 86ºF).
• Avoid excessive heat or humidity.

Inactive ingredients

Citric acid, D&C Red #40, FD&C Blue #1, flavor, glycerin, methylparaben, propylene glycol, propylparaben, purified water, sodium citrate, sucralose.

Questions or comments?

call weekdays from 8AM to 4PM AST at 1.787.608.0882

Contains the same active ingredients as Dometuss®-DMX*

SUGAR FREE

ALCOHOL FREE

Grape Flavor

Manufactured in USA with imported ingredients for ActiPharma. San Juan, PR 00917. www.actipharma.net.

* Dometuss® DMX is a registered trademark of Domel Laboratories. This product is not manufactured, distributed or marketed by Domel Laboratories.